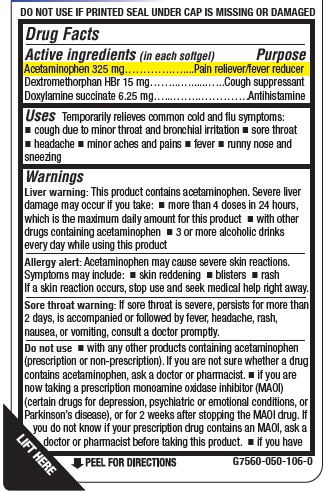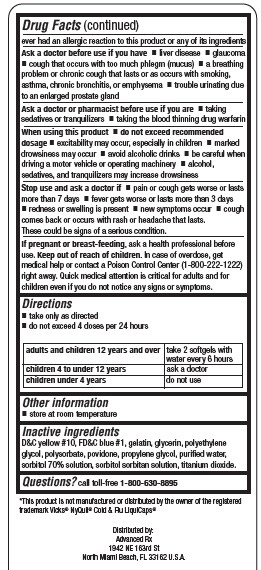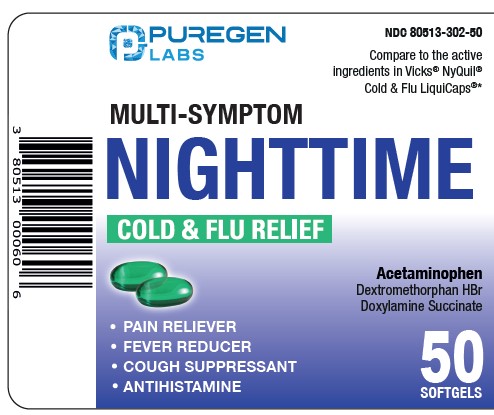 DRUG LABEL: NIGHTTIME COLD AND FLU RELIEF SOFTGELS

NDC: 80513-302 | Form: CAPSULE, GELATIN COATED
Manufacturer: Advanced Rx LLC
Category: otc | Type: HUMAN OTC DRUG LABEL
Date: 20240913

ACTIVE INGREDIENTS: DEXTROMETHORPHAN HYDROBROMIDE 15 mg/1 1; DOXYLAMINE SUCCINATE 6.25 mg/1 1; ACETAMINOPHEN 325 mg/1 1
INACTIVE INGREDIENTS: PROPYLENE GLYCOL; SORBITAN; FD&C BLUE NO. 1; POLAWAX POLYSORBATE; D&C YELLOW NO. 10; POVIDONE; TITANIUM DIOXIDE; GLYCERIN; GELATIN TYPE B BOVINE (160 BLOOM); POLYETHYLENE GLYCOL, UNSPECIFIED; WATER; SORBITOL SOLUTION

Advanced Rx - PUREGEN - MULTI-SYMPTOM NIGHTTIME COLD & FLU RELIEF (80513-302)

ACTIVE INGREDIENT (IN EACH SOFTGEL)

Acetaminophen 325 mg
Dextromethorphan HBr 15 mg
Doxylamine Succinate 6.25 mg

PURPOSE

Pain reliever/fever reducer
Cough suppressant
Antihistamine

USES

Temporarily relieves common cold and flu symptoms:

- cough due to minor throat and bronchial irritation
- sore throat
- headache
- minor aches and pains
- fever
- runny nose and sneezing

WARNINGS

Liver warning: This product contains acetaminophen. Severe liver damage may occur if you take:

- more than 4 doses in 24 hours, which is the maximum daily amount for this product
- with other drugs containing acetaminophen
- 3 or more alcoholic drinks every day while using this product

Allergy alert: Acetaminophen may cause severe skin reactions. Symptoms may include:

- skin reddening
- blisters
- rash

If a skin reaction occurs, stop use and seek medical help right away.

Sore throat warning: If sore throat is severe, persists for more than 2 days, is accompanied or followed by fever, headache, rash,
nausea, or vomiting, consult a doctor promptly.

Do not use

- with any other products containing acetaminophen (prescription or non-prescription). If you are not sure whether a drug

contains acetaminophen, ask a doctor or pharmacist.

if you are now taking a prescription monoamine oxidase inhibitor (MAOI) (certain drugs for depression, psychiatric or emotional conditions, or Parkinson’s disease), or for 2 weeks after stopping the MAOI drug. If you do not know if your prescription drug contains an MAOI, ask a doctor or pharmacist before taking this product.

- if you have ever had an allergic reaction to this product or any of its ingredients

Ask a doctor before use if you have

- liver disease
- glaucoma
- cough that occurs with too much phlegm (mucus)
- a breathing problem or chronic cough that lasts or as occurs with smoking, asthma, chronic bronchitis, or emphysema
- trouble urinating due to an enlarged prostate gland

Ask a doctor or pharmacist before use if you are

- taking sedatives or tranquilizers
- taking the blood thinning drug warfarin

When using this product

- do not exceed recommended dosage
- excitability may occur, especially in children
- marked drowsiness may occur
- avoid alcoholic drinks
- be careful when driving a motor vehicle or operating machinery
- alcohol, sedatives, and tranquilizers may increase drowsiness

Stop use and ask a doctor if

- pain or cough gets worse or lasts more than 7 days
- fever gets worse or lasts more than 3 days
- redness or swelling is present
- new symptoms occur
- cough comes back or occurs with rash or headache that lasts.

These could be signs of a serious condition.

If pregnant or breast-feeding, ask a health professional before use.

Keep out of reach of children. In case of overdose, get medical help or contact a Poison Control Center (1-800-222-1222) right away. Quick medical attention is critical for adults and for children even if you do not notice any signs or symptoms.

DIRECTIONS

- take only as directed
- do not exceed 4 doses per 24 hours

adults and children 12 years and over | take 2 softgels with water every 6 hours
children 4 to under 12 years | ask a doctor
children under 4 years | do not use

OTHER INFORMATION

- store at room temperature

INACTIVE INGREDIENTS

D&C yellow #10, FD&C blue #1, gelatin, glycerin, polyethylene glycol, polysorbate, povidone, propylene glycol, purified water, sorbitol 70% solution, sorbitol sorbitan solution, titanium dioxide.

QUESTIONS?

call toll-free 1-800-630-8895